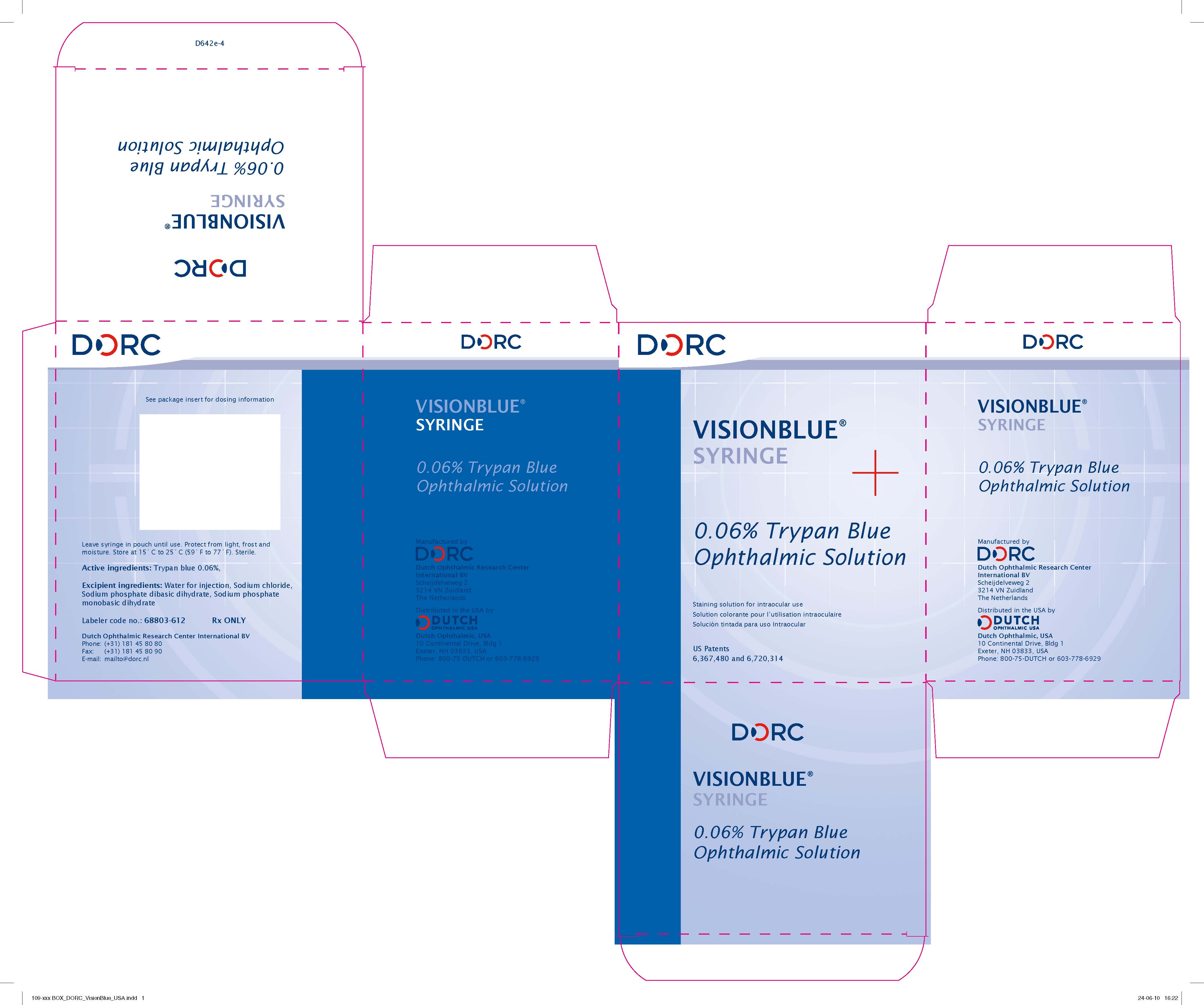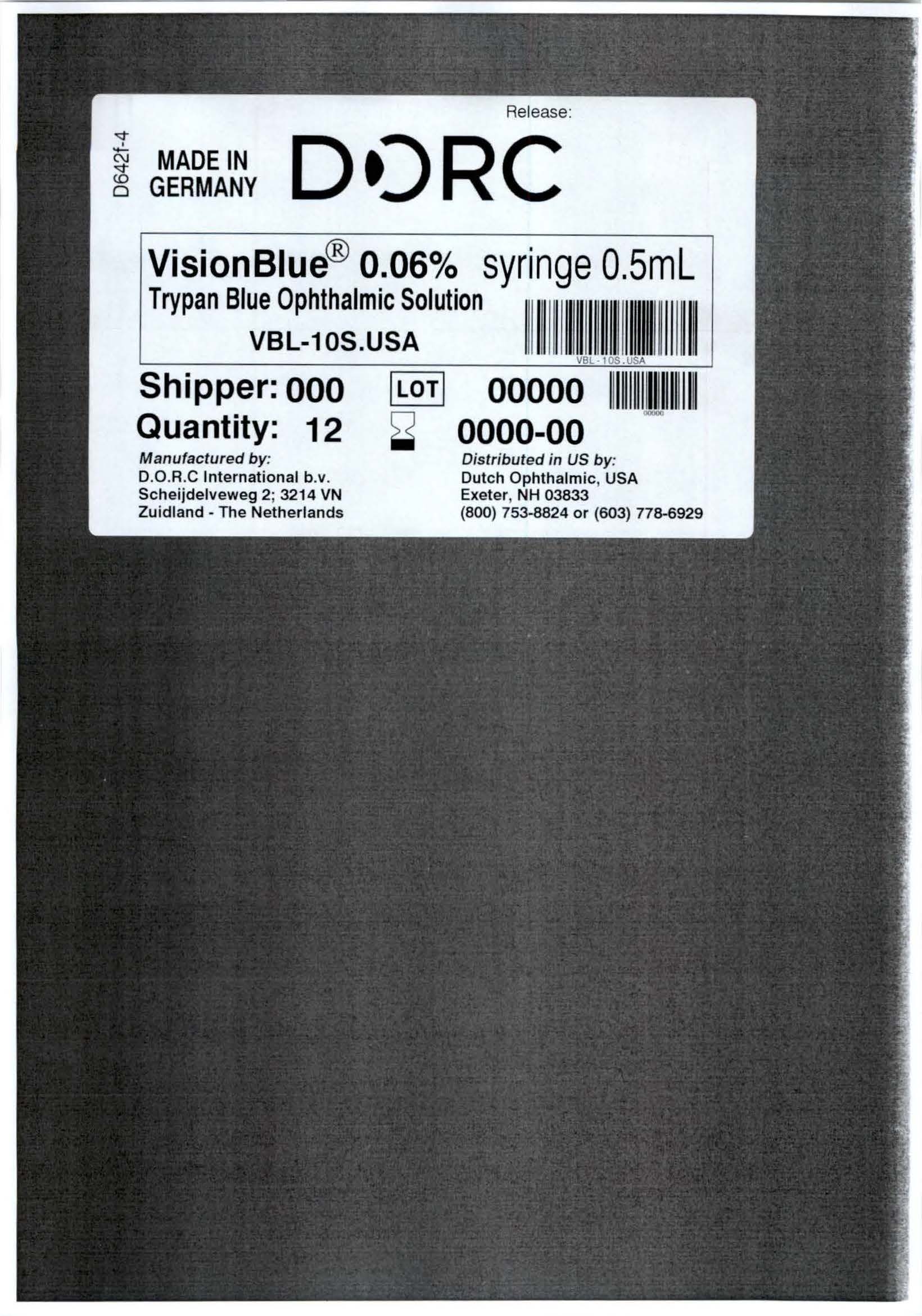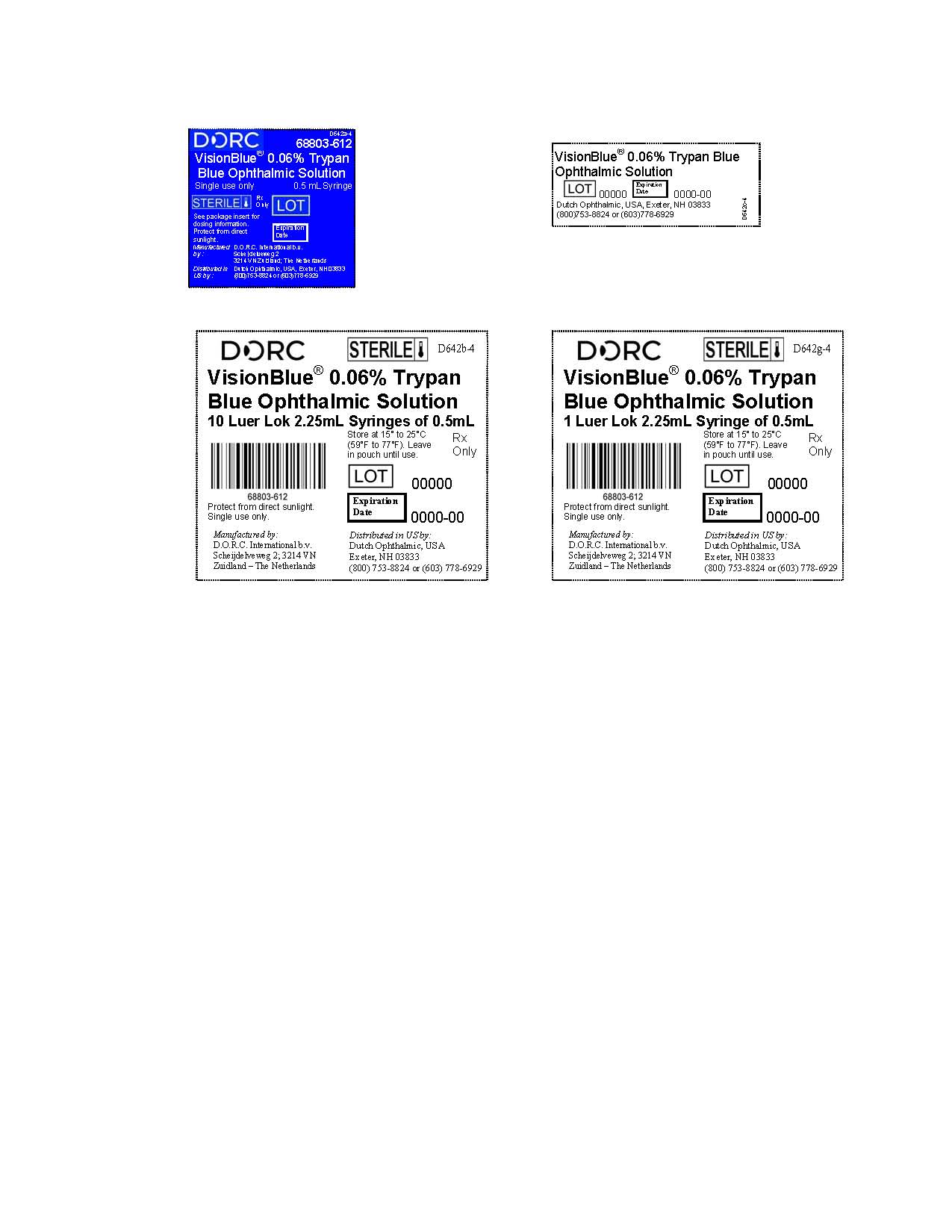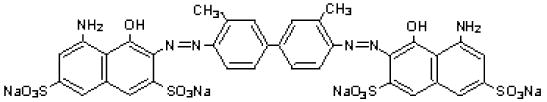 DRUG LABEL: VISIONBLUE
NDC: 68803-612 | Form: INJECTION, SOLUTION
Manufacturer: D.O.R.C. Dutch Ophthalmic Research Center (International) B.V.
Category: prescription | Type: HUMAN PRESCRIPTION DRUG LABEL
Date: 20231218

ACTIVE INGREDIENTS: TRYPAN BLUE 0.3 mg/0.5 mL
INACTIVE INGREDIENTS: SODIUM PHOSPHATE, MONOBASIC, DIHYDRATE 0.15 mg/0.5 mL; SODIUM PHOSPHATE, DIBASIC, DIHYDRATE 0.85 mg/0.5 mL; SODIUM CHLORIDE 4.1 mg/0.5 mL; WATER 0.5 mL/0.5 mL

HIGHLIGHTS OF PRESCRIBING INFORMATION

VisionBlue® 0.06% Trypan blue Ophthalmic Solution. These highlights do not include all the information needed to use VISIONBLUE® 0.06% safely and effectively. see full prescribing information for VISIONBLUE® 0.06%. VisionBlue® (trypan blue ophthalmic solution) 0.06% Initial U.S. Approval: 2004

VisionBlue 0.06% - Indications & Usage Section

HIGHLIGHTS OF PRESCRIBING INFORMATION

These highlights do not include all the information needed to use VISIONBLUE® safely and effectively. See full prescribing information for VISIONBLUE®. VisionBlue® (trypan blue ophthalmic solution) 0.06% Initial U.S. Approval: 2004

VisionBlue® 0.06% is a diagnostic dye indicated for use as an aid in ophthalmic surgery by staining the anterior capsule of the lens.

VisionBlue 0.06% - Dosage & Administration Section

- Inject an air bubble into the anterior chamber;
- Carefully apply VisionBlue® 0.06% onto the lens capsule;
- Remove all excess dye from the anterior chamber.

VisionBlue 0.06% - Dosage forms & Strengths section

VisionBlue® (trypan blue ophthalmic solution) 0.06% in a single-patient-use syringe.

VisionBlue 0.06% - Contraindications section

Insertion of a non-hydrated (dry-state), hydrophilic acrylic intraocular lens (IOL).

VisionBlue 0.06% - Warnings and Precautions section

Excessive staining: Excess VisionBlue® 0.06% should be removed from the eye immediately after staining.

VisionBlue 0.06% - Adverse Reactions section

Inadvertent staining of the posterior lens capsule and vitreous face.

To report SUSPECTED ADVERSE REACTIONS contact, Dutch Ophtalmic, USA at 1-800-75-DUTCH or FDA at 1-800-FDA-1088 or www.fda.gov/medwatch

FULL PRESCRIBING INFORMATION

VisionBlue 0.06% - Indications & Usage Section

VisionBlue® 0.06% is indicated for use as an aid in ophthalmic surgery by staining the anterior capsule of the lens.

VisionBlue 0.06% - Dosage & Administration Section

Cataract surgery.

VisionBlue® 0.06% is packaged in a single-patient-use syringe filled to a volume of 0.5 mL syringe to which a blunt cannula has to be attached.

After opening the eye, an air bubble is injected into the anterior chamber of the eye in order to minimize dilution of VisionBlue® 0.06% by the aqueous. VisionBlue® 0.06% is carefully applied onto the anterior lens capsule using a blunt cannula. Sufficient staining is achieved as soon as the dye has contacted the capsule. The anterior chamber is then irrigated with balanced salt solution to remove all excess dye. An anterior capsulotomy can then be performed.

VisionBlue 0.06% - Dosage forms & Strengths section

VisionBlue® (trypan blue ophtalmic solution) 0.06% is a clear, dark blue ophtalmic solution supplied in 2.25 mL single-patient-use syringe filled to a volume of 0.5 mL.

VisionBlue 0.06% - Contraindications section

VisionBlue® 0.06% is contraindicated when a non-hydrated (dry state), hydrophilic acrylic intraocular lens (IOL) is planned to be inserted into the eye. The dye may be absorbed by the IOL and stain it.

VisionBlue 0.06% - Warnings and Precautions section

Excessive staining:

It is recommended that after injection all excess VisionBlue® 0.06% is immediately removed from the eye by thorough irrigation of the anterior chamber.

VisionBlue 0.06% - Adverse Reactions section

Adverse reactions reported following use of VisionBlue® 0.06% include discoloration of high water content hydrogen intraocular lenses (see Contraindications) and inadvertent staining of the posterior lens capsule and vitreous face. Staining of the posterior lens capsule or staining of the vitreous face is generally self limited, lasting up to one week.

VisionBlue 0.06% - Use in specific populations section

VisionBlue 0.06% - Pregnancy section

Risk Summary

There are no available data on the use of VisionBlue® 0.06% in pregnant women to inform a drug-associated risk of major birth defects, miscarriage, or adverse maternal or fetal outcomes. Systemic absorption of VisionBlue® 0.06% in humans is expected to be negligible following injection and subsequent removal of the drug at the completion of surgical procedures. Adequate animal reproduction studies were not conducted with VisionBlue® 0.06%, however, trypan blue has been shown to be teratogenic in various animal models at doses 800-fold and greater than the maximum recommended human dose, based on body surface area (BSA).

Due to the negligible human systemic exposure when used as recommended, it is not expected that maternal use of VisionBlue® 0.06% will result in fetal exposure to the drug and risk of teratogenic effects.

Animal Data

Trypan blue is teratogenic in rats, mice, rabbits, hamsters, dogs, guinea pigs, pigs, and chickens. The majority of teratogenicity studies performed involve intravenous, intraperitoneal, or subcutaneous administration in the rat. The teratogenic dose is 50 mg/kg as a single dose or 25 mg/kg/day during embryogenesis in the rat. Normalized to BSA, these doses are approximately 1,600- and 800-fold the maximum recommended human dose of 0.3 mg per injection (based on a 60 kg person), assuming complete systemic absorption of trypan blue. Characteristic anomalies included neural tube, cardiovascular, vertebral, tail, and eye defects. Trypan blue also caused an increase in post-implantation mortality and decreased fetal weight. In the monkey, trypan blue caused abortions with single or two daily doses of 50 mg/kg between 20th to 25th days of pregnancy, but no apparent increase in birth defects (approximately 3,200-fold the maximum recommended human dose based on BSA, assuming total absorption).

VisionBlue 0.06% - Nursing Mothers section

Risk Summary

The presence of trypan blue in human milk following intraocular administration of trypan blue has not been evaluated. There are no data available regarding the effects of trypan blue on milk production. Breastfeeding is not expected to result in exposure of the child to trypan blue due to the negligible systemic exposure of trypan blue in humans following injection and subsequent removal of the drug at the completion of surgical procedures.

VisionBlue 0.06% - Pediatric use section

The safety and effectiveness of trypan blue have been established in pediatric patients. Use of trypan blue is supported by evidence from an adequate and well-controlled study in pediatric patients.

VisionBlue 0.06% - Geriatric use section

No overall differences in safety and effectiveness have been observed between elderly and younger patients.

VisionBlue 0.06% - Description section

VisionBlue® (trypan blue ophthalmic solution) 0.06% is a sterile solution of trypan blue (an acid di-azo group dye) for intraocular ophtalmic use. VisionBlue® 0.06% is a selective tissue staining agent for use as a medical aid in ophthalmic surgery.

Each mL of VisionBlue® 0.06% contains: 0.6 mg trypan blue; 1.9 mg sodium mono-hydrogen orthophosphate (Na2HPO4·2H2O); 0.3 mg sodium di-hydrogen orthophosphate (NaH2PO4·2H2O); 8.2 mg sodium chloride (NaCl); and water for injection. Sodium hydroxide may be used to adjust pH. The pH is 7.3 – 7.6. The osmolality is 257-314 mOsm/kg.

The drug substance trypan blue has the chemical name 3,3’-[(3,3’-dimethyl-4,4’-biphenylylene) bis (azo)] bis (5-amino-4-hydroxy-2,7-naphthalenedisulfonic acid) tetra sodium salt, a molecular weight of 960.8, a molecular formula of C34H24N6Na4O14S4, and has the following chemical structure:

VisionBlue 0.06% - Clinical Pharmacology section

VisionBlue 0.06% - Mechanism of action section

VisionBlue® 0.06% selectively stains connective tissue structures in the human eye such as the anterior lens capsule of the human crystalline lens.

VisionBlue® 0.06% is intended to be applied directly on the anterior lens capsule, staining any portion of the capsule which comes in contact with the dye. Excess dye is washed out of the anterior chamber. The dye does not penetrate the capsule, permitting visualization of the anterior capsule in contrast to the non-stained lens cortex and inner lens material.

VisionBlue 0.06% - Nonclinical toxicology section

Carcinogenesis, mutagenesis, impairment of fertility

VisionBlue 0.06% - Carcinogenesis & Mutagenesis & Impairment of fertility section

Trypan blue is carcinogenic in rats. Wistar/Lewis rats developed lymphomas after receiving subcutaneous injections of 1% trypan blue dosed at 50 mg/kg every other week for 52 weeks (total does approximately 42,000-fold the maximum recommended human dose of 0.3 mg per injection in a 60 kg person based on BSA, assuming total absorption).

Trypan blue was mutagenic in the Ames test and caused DNA strand breaks in vitro.

VisionBlue 0.06% - How supplied section

VisionBlue® 0.06% is a clear, dark blue ophtalmic solution supplied as follows:

0.5 mL of VisionBlue® 0.06% in a sterile single-patient-use Luer Lok, 2.25 mL glass syringe, grey rubber plunger stopper and tip cap with polypropylene plunger rod in a peel pouch. Ten pouched products are packed in one distribution box.

NDC 68803-612-05 (One 0,5 mL syringe)

NDC 68803-612-10 (Carton of ten 0.5 mL syringes)

VisionBlue 0.06% - Storage and Handling section

Store between 15-25°C (59-77°F). Protect form direct sunlight.

VisionBlue 0.06% - Patient counseling information

Advise patients that if a non-hydrated, hydrophilic acrylic intraocular lens (IOL) is inserted into their eye, it may absorb the dye and become stained.

Manufactured by

D.O.R.C. International b.v.

Scheijdelveweg 2

3214 VN Zuidland

The Netherlands

Distributed in the United States by

Dutch Ophthalmic, USA

10 Continental Drive, Bldg 1

Exeter, NH 03833, USA

Phone: 800-75-DUTCH of 603-778-6929

US Patents 6,367,480 and 6,720,314

Copyright ©, 2012 Dutch Ophthalmic Research Center